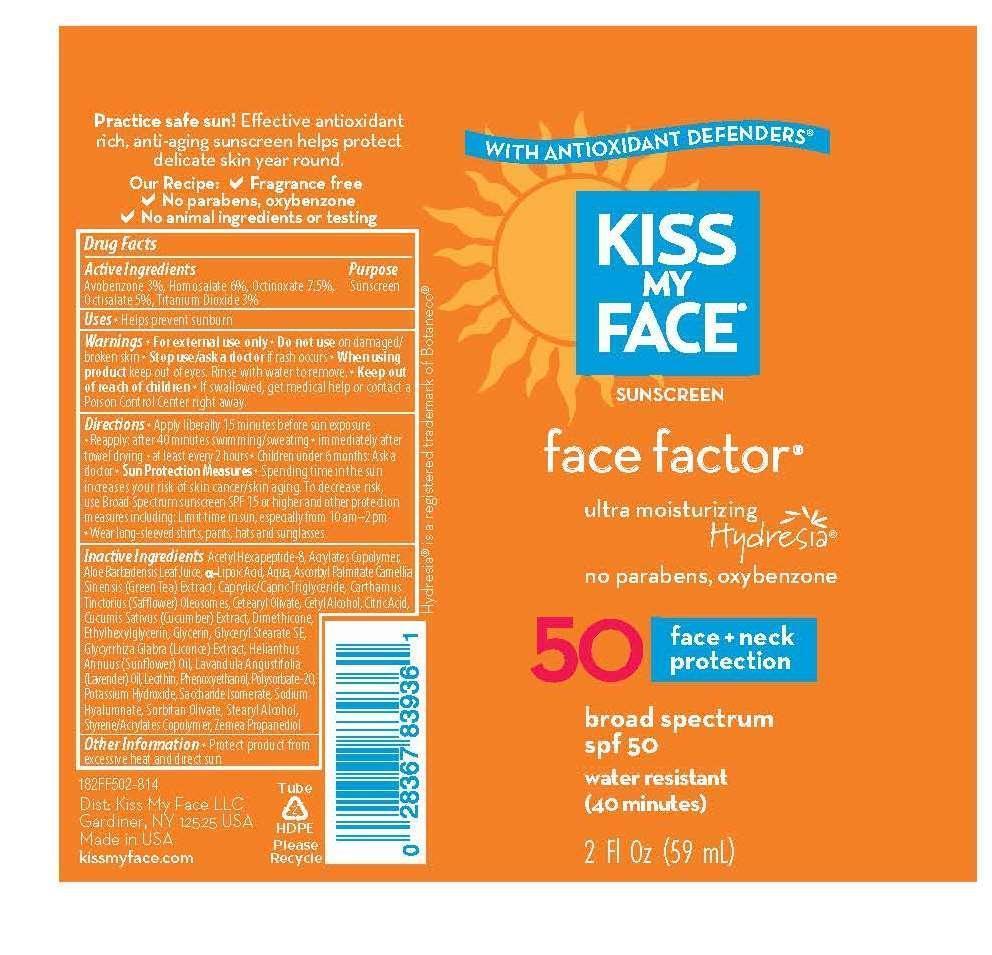 DRUG LABEL: Face Factor
NDC: 65364-219 | Form: LOTION
Manufacturer: Kiss My Face, LLC
Category: otc | Type: HUMAN OTC DRUG LABEL
Date: 20150123

ACTIVE INGREDIENTS: AVOBENZONE 3 g/100 g; HOMOSALATE 6 g/100 g; OCTINOXATE 7.5 g/100 g; OCTISALATE 5 g/100 g; TITANIUM DIOXIDE 3 g/100 g
INACTIVE INGREDIENTS: ACETYL HEXAPEPTIDE-8; DIMETHYLAMINOETHYL METHACRYLATE - BUTYL METHACRYLATE - METHYL METHACRYLATE COPOLYMER; .ALPHA.-LIPOIC ACID; WATER; GREEN TEA LEAF; ALOE VERA LEAF; ASCORBYL PALMITATE; CAPRYLIC/CAPRIC/LAURIC TRIGLYCERIDE; CARTHAMUS TINCTORIUS (SAFFLOWER) OLEOSOMES; CETOSTEARYL ALCOHOL; CETEARYL OLIVATE; CITRIC ACID ACETATE; CUCUMIS SATIVUS LEAF; DIMETHICONE; ETHYLHEXYLGLYCERIN; GLYCERYL STEARATE SE; GLYCERIN; LICORICE; SUNFLOWER OIL; LAVENDER OIL; LECITHIN, SOYBEAN; PHENOXYETHANOL; POLYSORBATE 20; POTASSIUM HYDROXIDE; SACCHARIDE ISOMERATE; HYALURONATE SODIUM; SORBITAN OLIVATE; STEARYL ALCOHOL; STYRENE/ACRYLAMIDE COPOLYMER (MW 500000); PROPANEDIOL

Face Factor

Active ingredients

Avobenzone (3.0%), Homosalate (6.0%), Octinoxate (7.5%), Octisalate (5.0%), Titanium Dioxide (3.0%).

Inactive ingredients

Acetyl Hexapeptide-8, Acrylates Copolymer, Aloe Barbadensis Leaf Juice, a-Lipoic Acid, Aqua, Ascorbyl Palmitate, Camellia Sinensis (Green Tea) Extract, Caprylic/Capric Triglyceride, Carthamus Tinctorius (Safflower) Oleosomes, Cetearyl Olivate, Cetyl Alcohol, Citric Acid, Cucumis Sativus (Cucumber) Extract, Dimethicone, Ethylhexylglycerin, Glycerin, Glyceryl Stearate SE, Glycrrhiza Glabra (Licorice) Extract, Helianthus Annuus (Sunflower) Oil, Lavandula Angustifolia (Lavender) Oil, Lecithin, Phenoxyethanol, Polysorbate-20, Potassium Hydroxide, Saccharide Isomerate, Sodium Hyaluronate, Sorbitan Olivate, Stearyl Alcohol, Styrene/Acrylate Copolymer, Zemea Propanediol.

Keep out of reach of children

Directions

Apply liberally 15 minutes before sun exposure

Reapply ater 40 minutes swimming/sweating, immediately after towel drying, and at least every 2 hours

Children under 6 months ask a doctor

Use

Helps prevent sunburn

Purpose

sunscreen

Warnings

For external use only

Do not use on damaged or broken skin

Stop use and ask doctor if rash occurs

When using this product keep out of eyes. Rinse with water to remove.

If swallowed get medical help or contact a poison control center right away